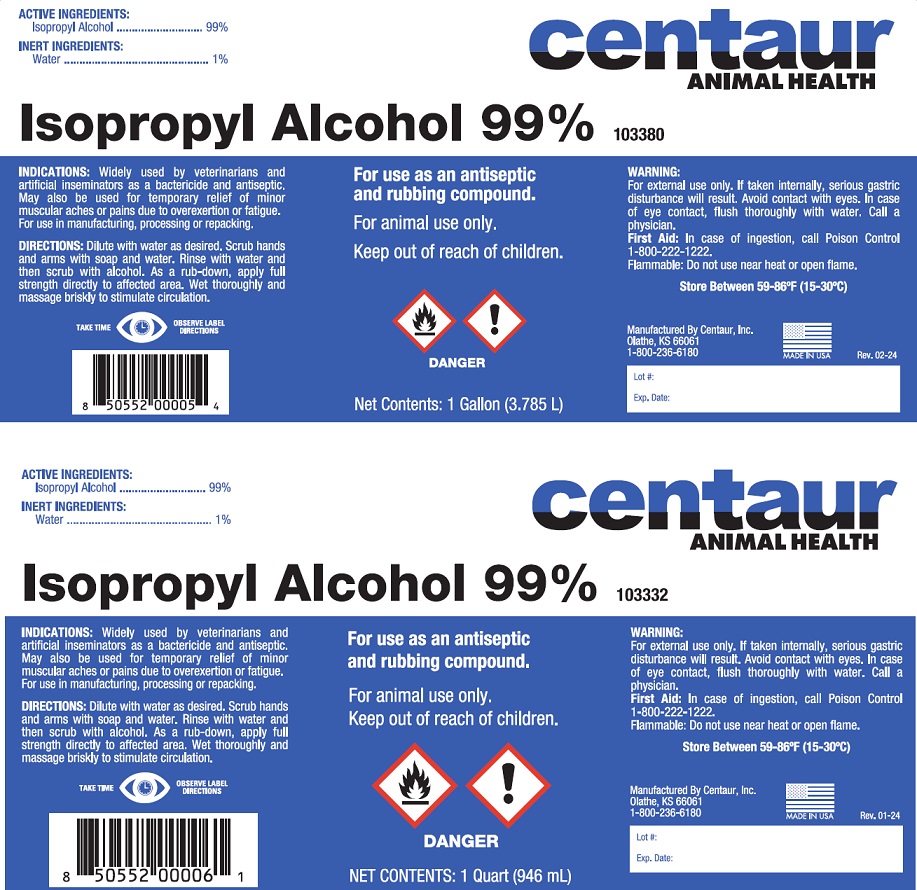 DRUG LABEL: Isopropyl Alcohol
NDC: 58305-033 | Form: LIQUID
Manufacturer: Centaur, Inc.
Category: animal | Type: OTC ANIMAL DRUG LABEL
Date: 20241023

ACTIVE INGREDIENTS: ISOPROPYL ALCOHOL 99 L/100 L
INACTIVE INGREDIENTS: WATER 1 L/100 L

Isopropyl Alcohol 99%

WARNINGS AND PRECAUTIONS

Isopropyl Alcohol 99%

For use as an antiseptic and rubbing compound.

For animal use only

Keep out of reach of children.

ACTIVE INGREDIENTS:

Isopropyl Alcohol ................. 99%

INERT INGREDIENTS:

Water .....................................1%

INDICATIONS: Widely used by veterinarians and artificial inseminators as a bactericide and antiseptic. May also be used for temporary relief of minor muscular aches or pains due to overexertion or fatigue. For use in manufacturing processing, or repacking, or repacking.

DIRECTIONS: Dilute with water as desired. Scrub hands and arms with soap and water. Rinse with water and then scrub with alcohol. As a rub down, apply full strength directly to affected area. Wet thoroughly and massage briskly to stimulate circulation.

WARNING: For external use only. If taken internally, serious gastric disturbance will result. Avoid contact with eyes. In case of eye contact, flush thoroughly with water. Call a physician.

First Aid: In case of ingestion, call Poison Control 1-800-222-1222.

Flammable: Do not use near heat or open flames.

Store Between 59-86°F (15-30°C)